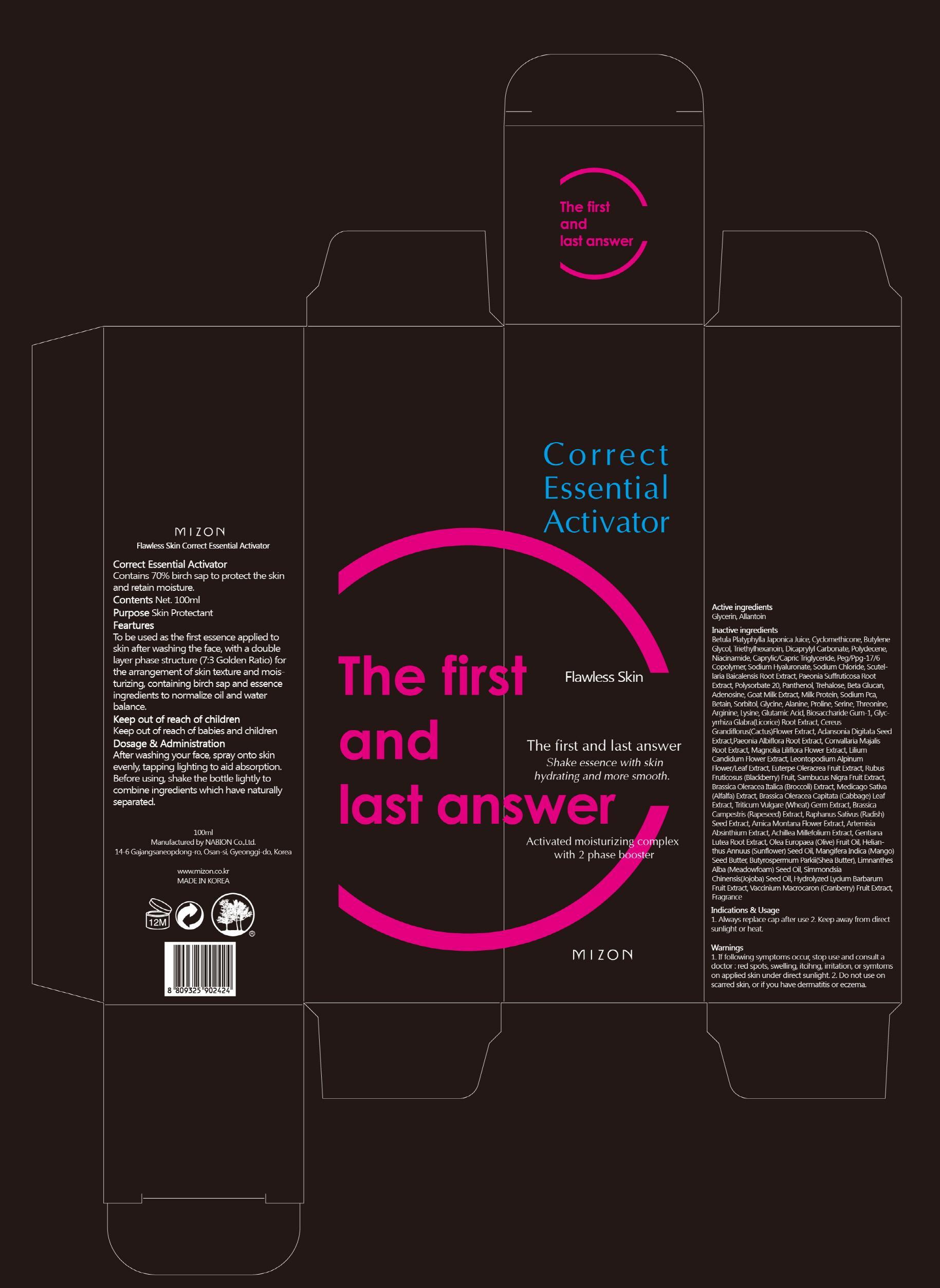 DRUG LABEL: CORRECT ESSENTIAL ACTIVATOR
NDC: 57718-010 | Form: CREAM
Manufacturer: MIZON CO., LTD.
Category: otc | Type: HUMAN OTC DRUG LABEL
Date: 20130503

ACTIVE INGREDIENTS: Glycerin 20 mg/100 mL; Allantoin 0.6 mg/100 mL
INACTIVE INGREDIENTS: WATER; BUTYLENE GLYCOL; TRIETHYLHEXANOIN

ACTIVE INGREDIENT

Active ingredients: Glycerin 20%, Allantoin 0.6%

INACTIVE INGREDIENT

Inactive ingredients:
Betula Platyphylla Japonica Juice, Cyclomethicone, Butylene Glycol, Triethylhexanoin, Dicaprylyl Carbonate, Polydecene, Niacinamide, Caprylic/Capric Triglyceride, Peg/Ppg-17/6 Copolymer, Sodium Hyaluronate, Sodium Chloride, Scutellaria Baicalensis Root Extract, Paeonia Suffruticosa Root Extract, Polysorbate 20, Panthenol, Trehalose, Beta Glucan, Adenosine, Goat Milk Extract, Milk Protein, Sodium Pca, Betain, Sorbitol, Glycine, Alanine, Proline, Serine, Threonine, Arginine, Lysine, Glutamic Acid, Biosaccharide Gum-1, Glycyrrhiza Glabra(Licorice) Root Extract, Cereus Grandiflorus(Cactus)Flower Extract, Adansonia Digitata Seed Extract,Paeonia Albiflora Root Extract, Convallaria Majalis Root Extract, Magnolia Liliflora Flower Extract, Lilium Candidum Flower Extract, Leontopodium Alpinum Flower/Leaf Extract, Euterpe Oleracrea Fruit Extract, Rubus Fruticosus (Blackberry) Fruit, Sambucus Nigra Fruit Extract, Brassica Oleracea Italica (Broccoli) Extract, Medicago Sativa (Alfalfa) Extract, Brassica Oleracea Capitata (Cabbage) Leaf Extract, Triticum Vulgare (Wheat) Germ Extract, Brassica Campestris (Rapeseed) Extract, Raphanus Sativus (Radish) Seed Extract, Arnica Montana Flower Extract, Artemisia Absinthium Extract, Achillea Millefolium Extract, Gentiana Lutea Root Extract, Olea Europaea (Olive) Fruit Oil, Helianthus Annuus (Sunflower) Seed Oil, Mangifera Indica (Mango) Seed Butter, Butyrospermum Parkii(Shea Butter), Limnanthes Alba (Meadowfoam) Seed Oil, Simmondsia Chinensis(Jojoba) Seed Oil, Hydrolyzed Lycium Barbarum Fruit Extract, Vaccinium Macrocaron (Cranberry) Fruit Extract, Fragrance

PURPOSE

Purpose: Skin Protectant

WARNINGS

1. If following symptoms occur, stop use and consult a doctor: red spots, swelling, itcihng, irritation, or symtoms on applied skin under direct sunlight.
2. Do not use on scarred skin, or if you have dermatitis or eczema.

KEEP OUT OF REACH OF CHILDREN

Keep out of reach of babies and children

INDICATIONS AND USAGE

1. Always replace cap after use
2. Keep away from direct sunlight or heat.

DOSAGE AND ADMINISTRATION

After washing your face, spray onto skin evenly, tapping lighting to aid absorption.
Before using, shake the bottle lightly to combine ingredients which have naturally separated.